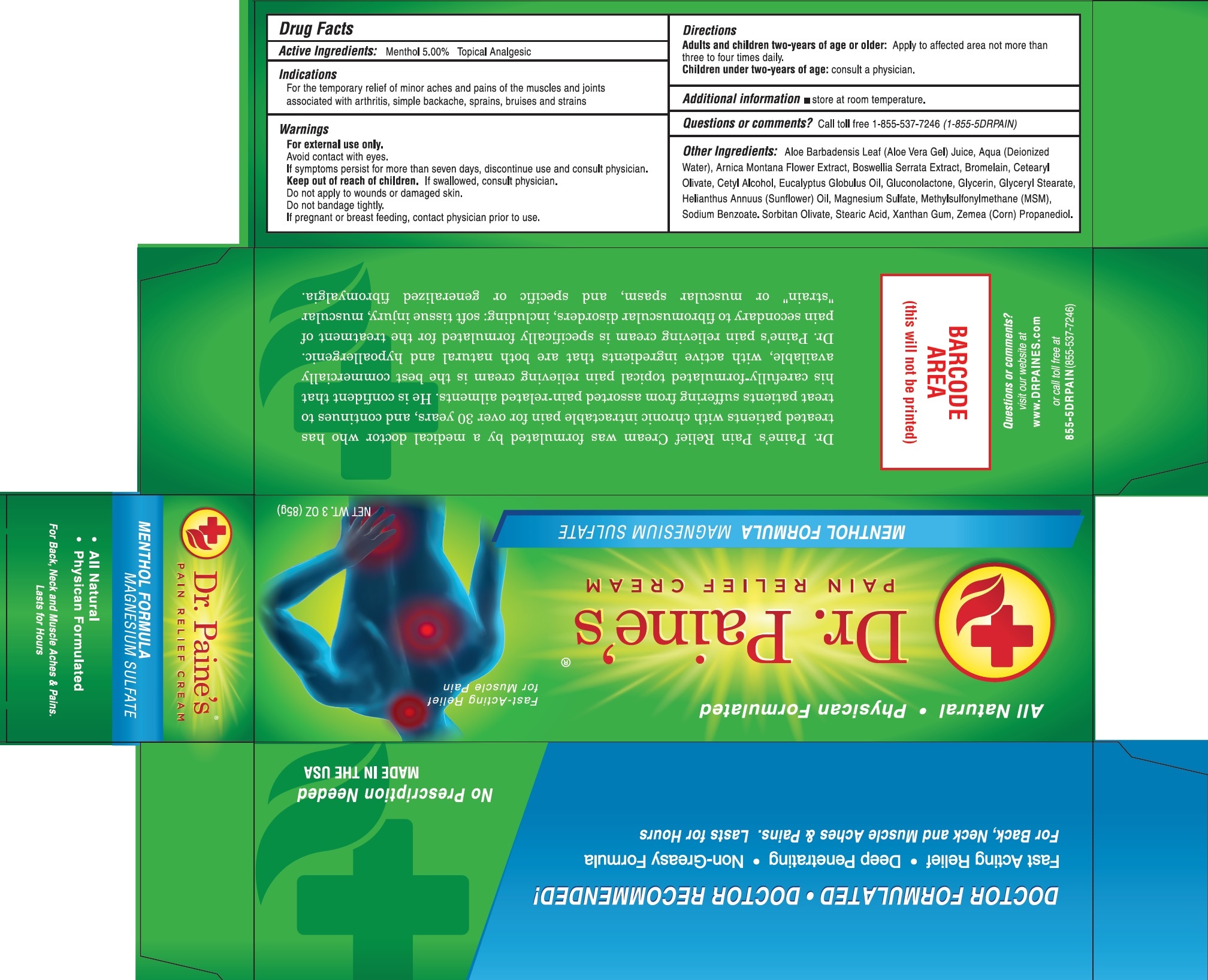 DRUG LABEL: Dr PAINES Pain Relief
NDC: 78970-161 | Form: CREAM
Manufacturer: DOCTOR PAINE'S MEDICAL, LLC
Category: otc | Type: HUMAN OTC DRUG LABEL
Date: 20231111

ACTIVE INGREDIENTS: MENTHOL 50 mg/1 g
INACTIVE INGREDIENTS: GLUCONOLACTONE; GLYCERIN; GLYCERYL MONOSTEARATE; HELIANTHUS ANNUUS FLOWERING TOP; MAGNESIUM SULFATE, UNSPECIFIED FORM; DIMETHYL SULFONE; SODIUM BENZOATE; SORBITAN OLIVATE; STEARIC ACID; XANTHAN GUM; CORN; PROPANEDIOL; ALOE VERA LEAF; WATER; ARNICA MONTANA FLOWER; INDIAN FRANKINCENSE; BROMELAINS; CETEARYL OLIVATE; CETYL ALCOHOL; EUCALYPTUS OIL

Dr. PAINE'S Pain Relief Cream

Active Ingredients:

Menthol 5.00%

PURPOSE

Topical Analgesic

Indications

For the temporary relief of minor aches and pains of the muscles and joints associated with arthritis, simple backache, sprains, bruises and strains

Warnings

For external use only.

Avoid contact with eyes.

If symptoms persist for more than seven days,discontinue use and consult physician.

Keep out of reach of children.

If swallowed, consult physician.

Do not

apply to wounds damaged skin.

Do not bandage tightly.

If pregnant or breast feeding,

contact physician prior to use.

Directions

Apply to affected area not more than three to four times daily. Adults and children two-years of age or older:

consult a physician. Children under two-years of age:

Additional information

store at room temperature.

Questions or comments?

Call toll free 1-855-537-7246 (1-855-5DRPAIN)

Other Ingredients:

Aloe Barbadensis Leaf (Aloe Vera Gel) Juice, Aqua (Deionized Water), Arnica Montana Flower Extract, Boswellia Serrata Extract, Bromelain, Cetearyl Olivate, Cetyl Alcohol, Eucalyptus Globulus Oil, Gluconolactone, Glycerin, Glyceryl Stearate, Helianthus Annuus (Sunflower) Oil, Magnesium Sulfate, Methylsulfonylmethane (MSM), Sodium Benzoate, Sorbitan Olivate, Stearic Acid, Xanthan Gum, Zemea (Corn) Propanediol.